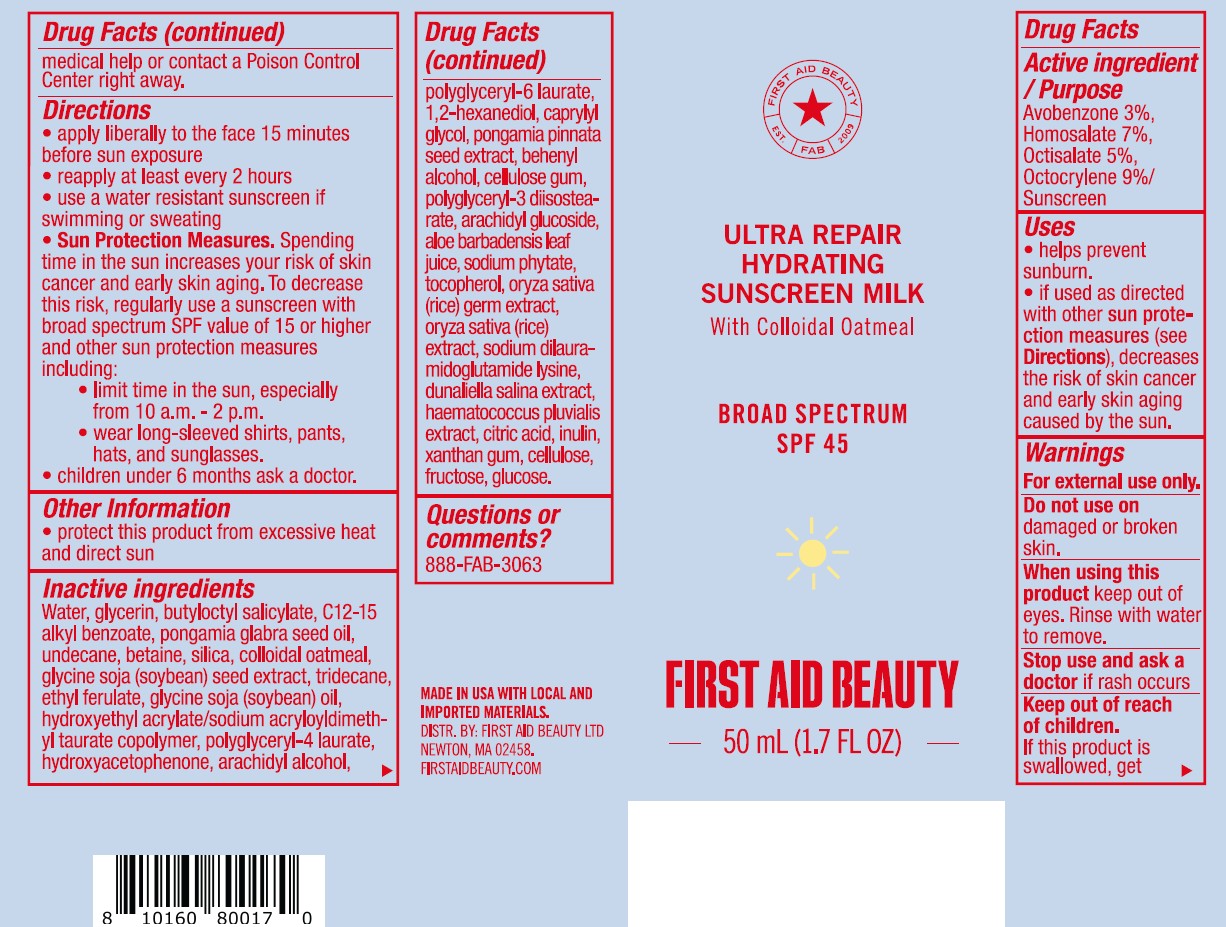 DRUG LABEL: First Aid Beauty Ultra Repair Hydrating Sunscreen Milk Broad Spectrum SPF 45
NDC: 84126-216 | Form: LOTION
Manufacturer: The Procter & Gamble Manufacturing Company
Category: otc | Type: HUMAN OTC DRUG LABEL
Date: 20260114

ACTIVE INGREDIENTS: OCTISALATE 5 g/100 mL; AVOBENZONE 3 g/100 mL; OCTOCRYLENE 9 g/100 mL; HOMOSALATE 7 g/100 mL
INACTIVE INGREDIENTS: TRIDECANE; SODIUM PHYTATE; POLYGLYCERYL-6 LAURATE; FRUCTOSE; ALOE BARBADENSIS LEAF JUICE; HYDROXYACETOPHENONE; ARACHIDYL GLUCOSIDE; RICE GERM; INULIN; HAEMATOCOCCUS PLUVIALIS; GLUCOSE; BETAINE; GLYCINE SOJA (SOYBEAN) SEED; DUNALIELLA SALINA; POWDERED CELLULOSE; POLYGLYCERYL-3 DIISOSTEARATE; UNDECANE; PONGAMIA PINNATA SEED; BEHENYL ALCOHOL; SOYBEAN OIL; ARACHIDYL ALCOHOL; OATMEAL; POLYGLYCERYL-4 LAURATE; 1,2-HEXANEDIOL; CELLULOSE GUM; CAPRYLYL GLYCOL; TOCOPHEROL; XANTHAN GUM; WATER; GLYCERIN; C12-15 ALKYL BENZOATE; CITRIC ACID; SODIUM DILAURAMIDOGLUTAMIDE LYSINE; HYDROXYETHYL ACRYLATE/SODIUM ACRYLOYLDIMETHYL TAURATE COPOLYMER (100000 MPA.S AT 1.5%); BUTYLOCTYL SALICYLATE; ETHYL FERULATE; PONGAMIA GLABRA SEED OIL; SILICA

First Aid Beauty Ultra Repair Hydrating Sunscreen Milk Broad Spectrum SPF 45

Drug Facts

ACTIVE INGREDIENT

Avobenzone 3%

Homosalate 7%

Octisalate 5%
Octocrylene 9%

PURPOSE

Sunscreen

Uses

- helps prevent sunburn
- if used as directed with other sun protection measures (see Directions), decreases the risk of skin cancer and early skin aging caused by the sun

Warnings

For external use only

Do not use

- on damaged or broken skin

When using this product

- keep out of eyes. Rinse with water to remove.

Stop use and ask a doctor if

- rash occurs

Keep out of reach of children. If product is swallowed, get medical help or contact a Poison Control Center right away.

Directions

- apply liberally 15 minutes before sun exposure
- reapply at least every 2 hours
- use water resistant sunscreen if swimming or sweating
- Sun Protection Measures. Spending time in the sun increases your risk of skin cancer and early skin aging. To decrease this risk, regularly use a sunscreen with a Broad Spectrum SPF value of 15 or higher and other sun protection measures including:
  - limit time in sun, especially from 10 a.m. - 2 p.m.
  - wear long-sleeved shirts, pants, hats, and sunglasses
- children under 6 months: ask a doctor

Other information

- protect this product from excessive heat and direct sun

Inactive ingredients

Water, glycerin, butyloctyl salicylate, C12-15 alkyl benzoate, pongamia glabra seed oil, undecane, betaine, silica, colloidal oatmeal, glycine soja (soybean) seed extract, tridecane, ethyl ferulate, glycine soja (soybean) oil, hydroxyethyl acrylate/sodium acryloyldimethyl taurate copolymer, polyglyceryl-4 laurate, hydroxyacetophenone, arachidyl alcohol, polyglyceryl-6 laurate, 1,2-hexanediol, caprylyl glycol, pongamia pinnata seed extract, behenyl alcohol, cellulose gum, polyglyceryl-3 diisostearate, arachidyl glucoside, aloe barbadensis leaf juice, sodium phytate, tocopherol, oryza sativa (rice) germ extract, oryza sativa (rice) extract, sodium dilauramidoglutamide lysine, dunaliella salina extract, haematococcus pluvialis extract, citric acid, inulin, xanthan gum, cellulose, fructose, glucose

Questions?

888-FAB-3063

MADE IN USA.

FIRST AID BEAUTY ® LTD
NEWTON, MA 02458.

WWW.FIRSTAIDBEAUTY.COM

PACKAGE LABEL

First Aid Beauty

Ultra Repair Hydrating Sunscreen Milk

with Colloidal Oatmeal

Broad Spectrum

SPF 45

FIRST AID BEAUTY

1.7 FL OZ (50 mL)